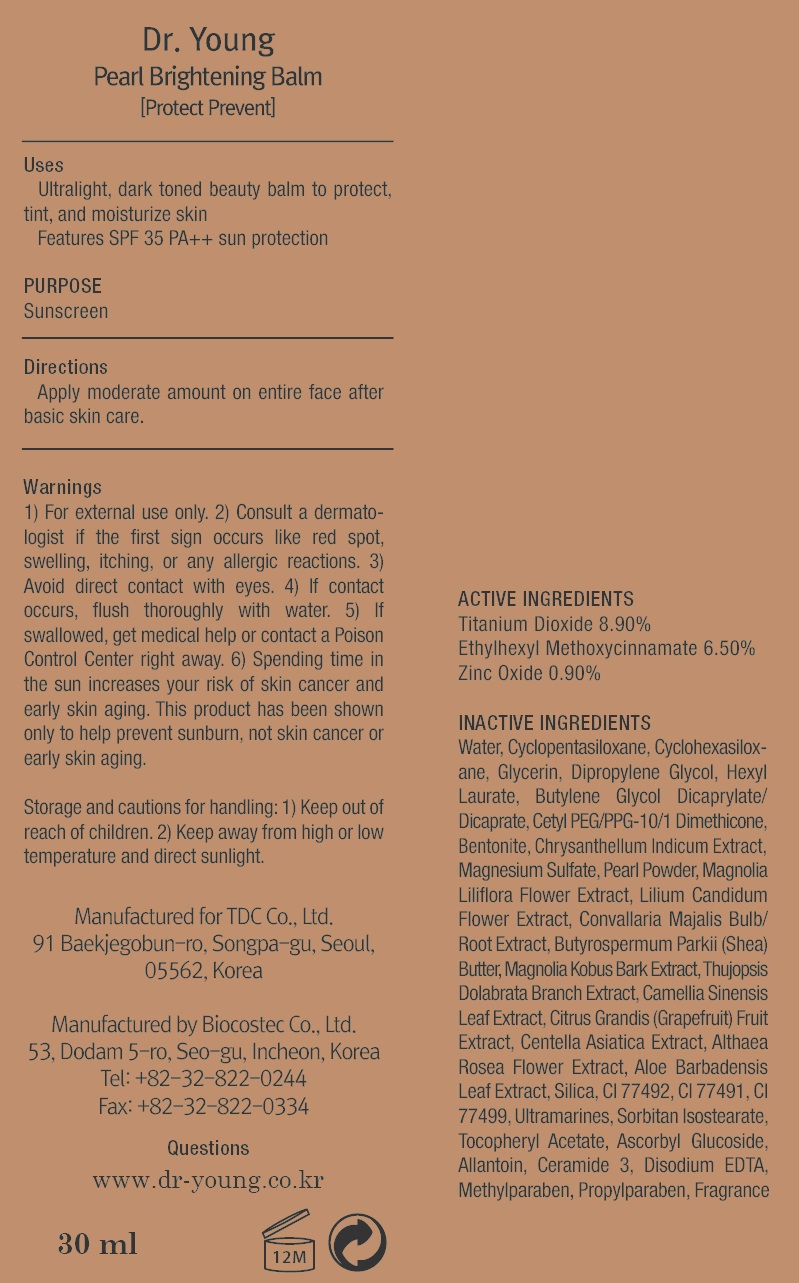 DRUG LABEL: Dr Young Protect Prevent 2P Pearl Brightening Balm
NDC: 43948-1310 | Form: CREAM
Manufacturer: Tdc, Co. Ltd
Category: otc | Type: HUMAN OTC DRUG LABEL
Date: 20181205

ACTIVE INGREDIENTS: Titanium Dioxide 2.67 g/30 mL; Octinoxate 1.95 g/30 mL; Zinc Oxide 0.27 g/30 mL
INACTIVE INGREDIENTS: Water; Glycerin

ACTIVE INGREDIENT

Active ingredients: Titanium Dioxide 8.90%, Ethylhexyl Methoxycinnamate 6.50%, Zinc Oxide 0.90%

INACTIVE INGREDIENT

Inactive ingredients: Water, Cyclopentasiloxane, Cyclohexasiloxane, Glycerin, Dipropylene Glycol, Hexyl Laurate, Butylene Glycol Dicaprylate/Dicaprate, Cetyl PEG/PPG-10/1 Dimethicone, Bentonite, Chrysanthellum Indicum Extract, Magnesium Sulfate, Pearl Powder, Magnolia Liliflora Flower Extract, Lilium Candidum Flower Extract, Convallaria Majalis Bulb/Root Extract, Butyrospermum Parkii (Shea) Butter, Magnolia Kobus Bark Extract, Thujopsis Dolabrata Branch Extract, Camellia Sinensis Leaf Extract, Citrus Grandis (Grapefruit) Fruit Extract, Centella Asiatica Extract, Althaea Rosea Flower Extract, Aloe Barbadensis Leaf Extract, Silica, CI 77492, CI 77491, CI 77499, Ultramarines, Sorbitan Isostearate, Tocopheryl Acetate, Ascorbyl Glucoside, Allantoin, Ceramide 3, Disodium EDTA, Methylparaben, Propylparaben, Fragrance

PURPOSE

Purpose: Sunscreen

WARNINGS

Warning: 1) For external use only. 2) Consult a dermatologist if the first sign occurs like red spot, swelling, itching, or any allergic reactions. 3) Avoid direct contact with eyes. 4) If contact occurs, flush thoroughly with water. 5) If swallowed, get medical help or contact a Poison Control Center right away. 6) Spending time in the sun increases your risk of skin cancer and early skin aging. This product has been shown only to help prevent sunburn, not skin cancer or early skin aging. Storage and cautions for handling: 1) Keep out of reach of children. 2) Keep away from high or low temperature and direct sunlight.

DESCRIPTION

Uses: - Ultralight, dark toned beauty balm to protect, tint, and moisturize skin - Features SPF 35 PA++ sun protection

Directions: Apply moderate amount on entire face after basic skin care.